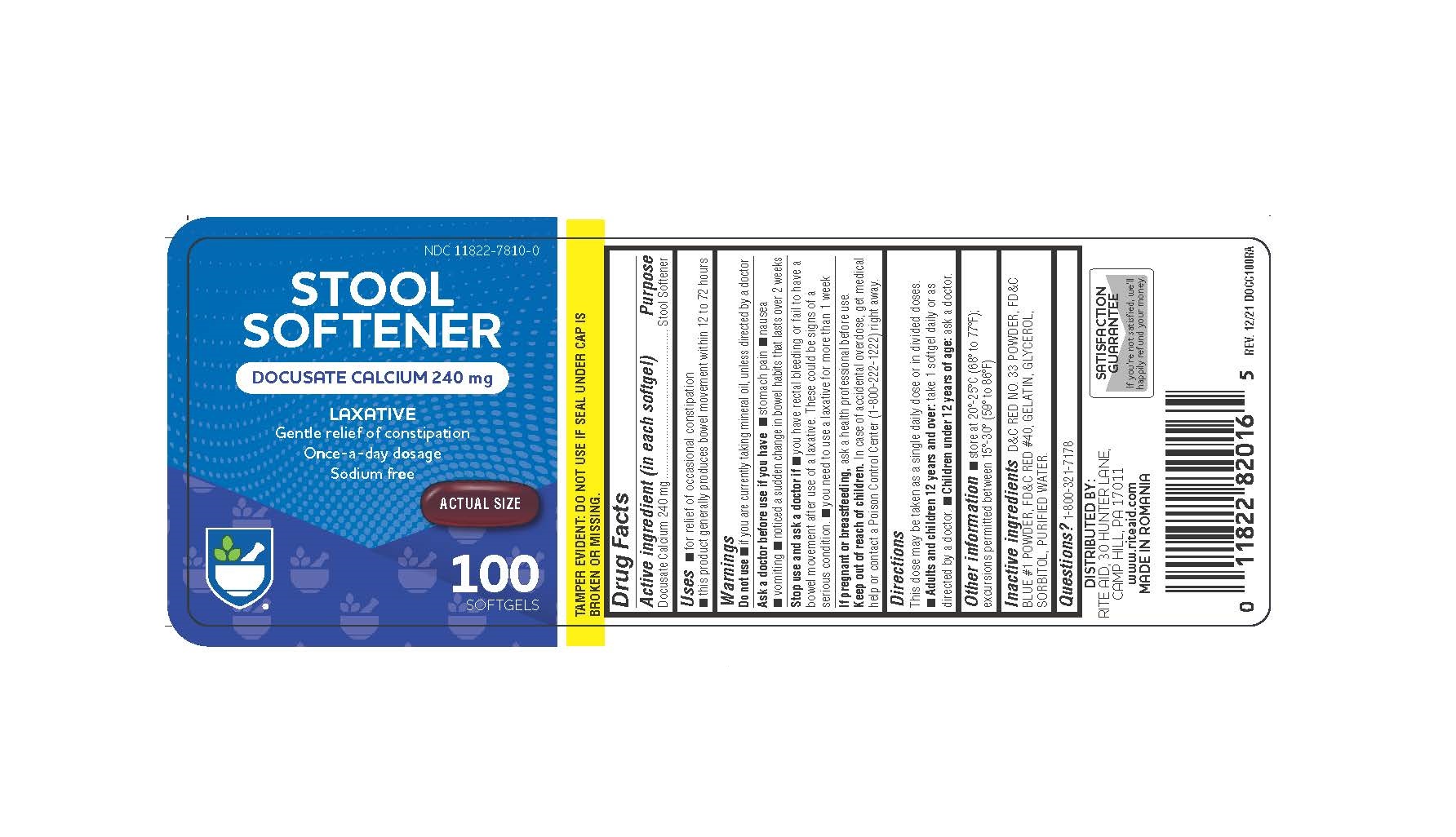 DRUG LABEL: Rite Aid Stool Softener
NDC: 11822-7810 | Form: CAPSULE, LIQUID FILLED
Manufacturer: Rite Aid
Category: otc | Type: HUMAN OTC DRUG LABEL
Date: 20241218

ACTIVE INGREDIENTS: DOCUSATE CALCIUM 240 mg/1 1
INACTIVE INGREDIENTS: GELATIN; GLYCERIN; SORBITOL; WATER; FD&C BLUE NO. 1; FD&C RED NO. 40

Docusate Calcium

Active ingredient

Docusate Calcium 240 mg

Purpose

Stool Softener

Uses

- For the relief of occasional constipation.
- This product generally produces a bowel movement within 12 to 72 hours.

Warnings: Do not use

- If you are currently taking mineral oil, unless directed by a doctor.
- When abdominal pain, nausea or vomiting are present.
- For longer than one week unless directed by a doctor.

Ask a Doctor Before Use

■ stomach pain ■ nausea ■ vomiting ■ noticed a sudden change in bowel habits that lasts over 2 weeks

Stop Use and Ask a Doctor If

- You have rectal bleeding.
- You fail to have a bowel movement after use.

If Pregnant or Breast Feeding

Ask a healthcare professional before use.

Keep Out of Reach of Children.

In case of accidental overdose, get medical help or contact a Poison Control Center (1-800-222-1222) right away.

Directions

Adults and Children over 12 years of age

Take orally 1 softgel daily for 2 to 3 days or until bowl movements are normal, or as directed by a doctor.

Children under 12 years of age

Do not use this product for children under 12 years of age, unless directed by a doctor.

Other Information

- Store at room temperature between 15ºC to 25ºC (59ºF to 77ºF).
- Do not use if either seal is broken or missing.

Inactive Ingredients

FD&C Blue #1, FD&C Red #40, Gelatin, Glycerin, Sorbitol Special.